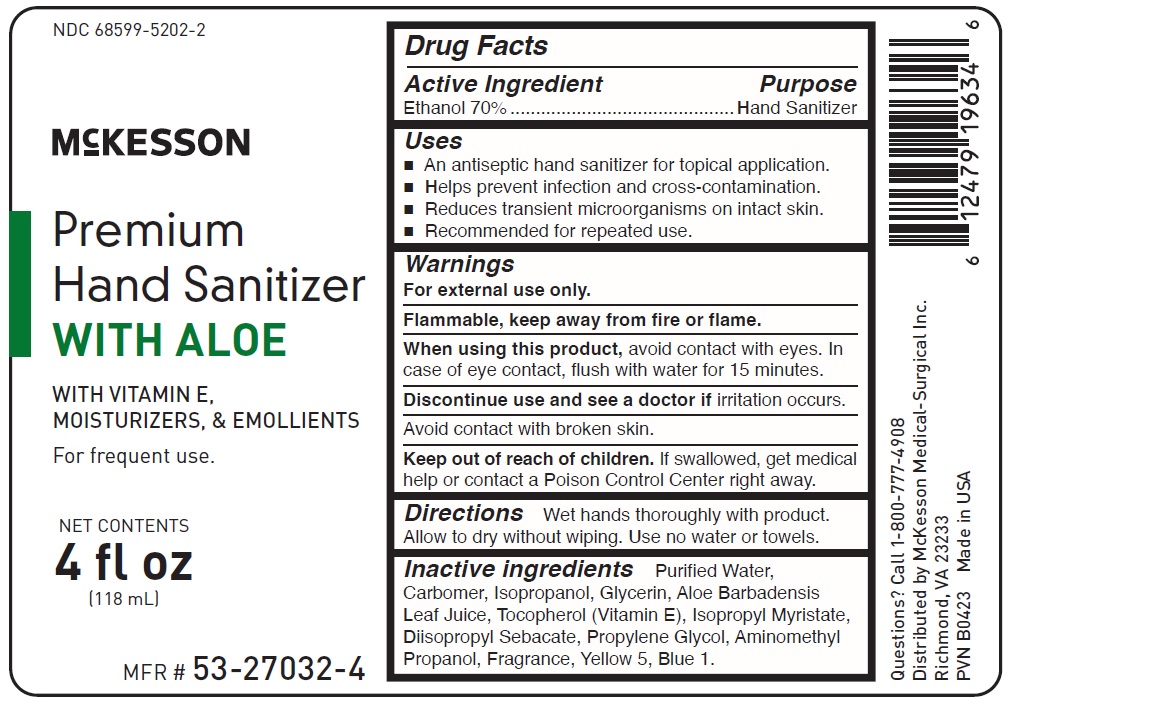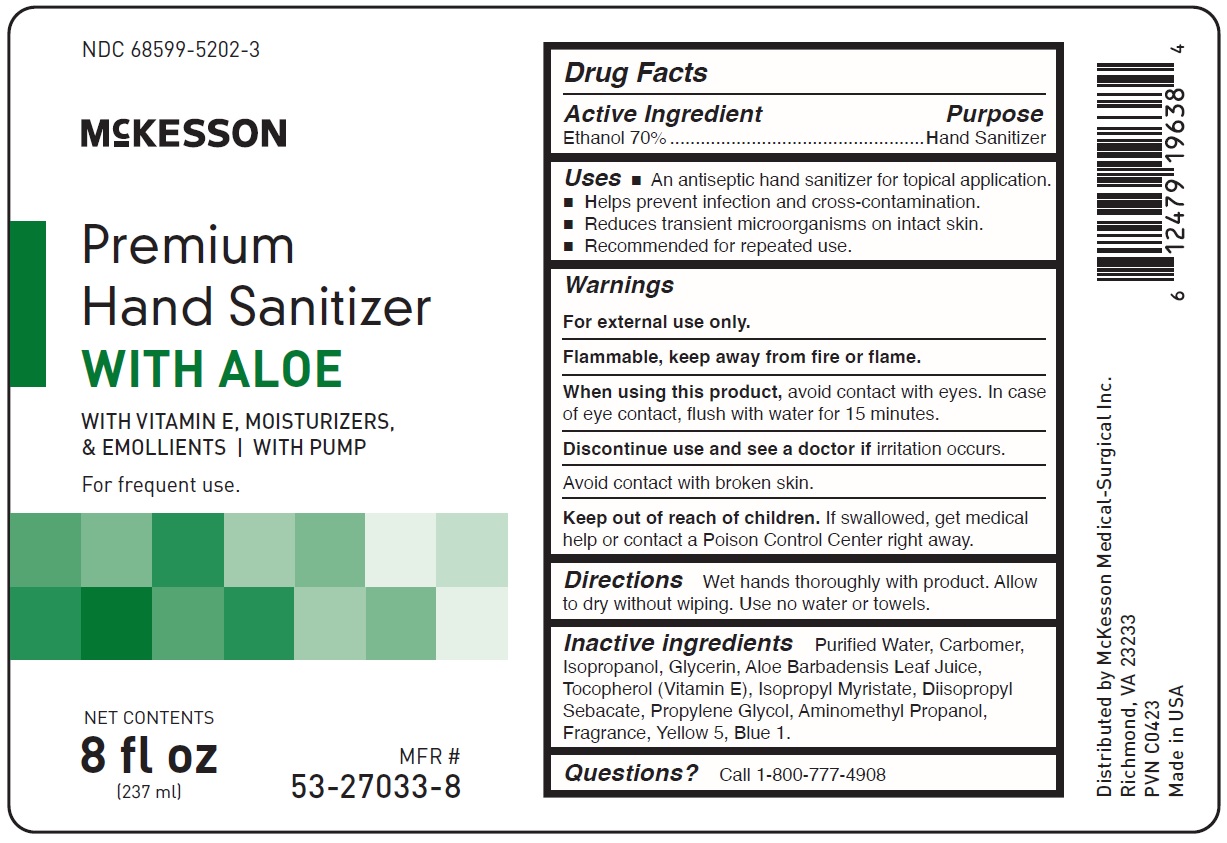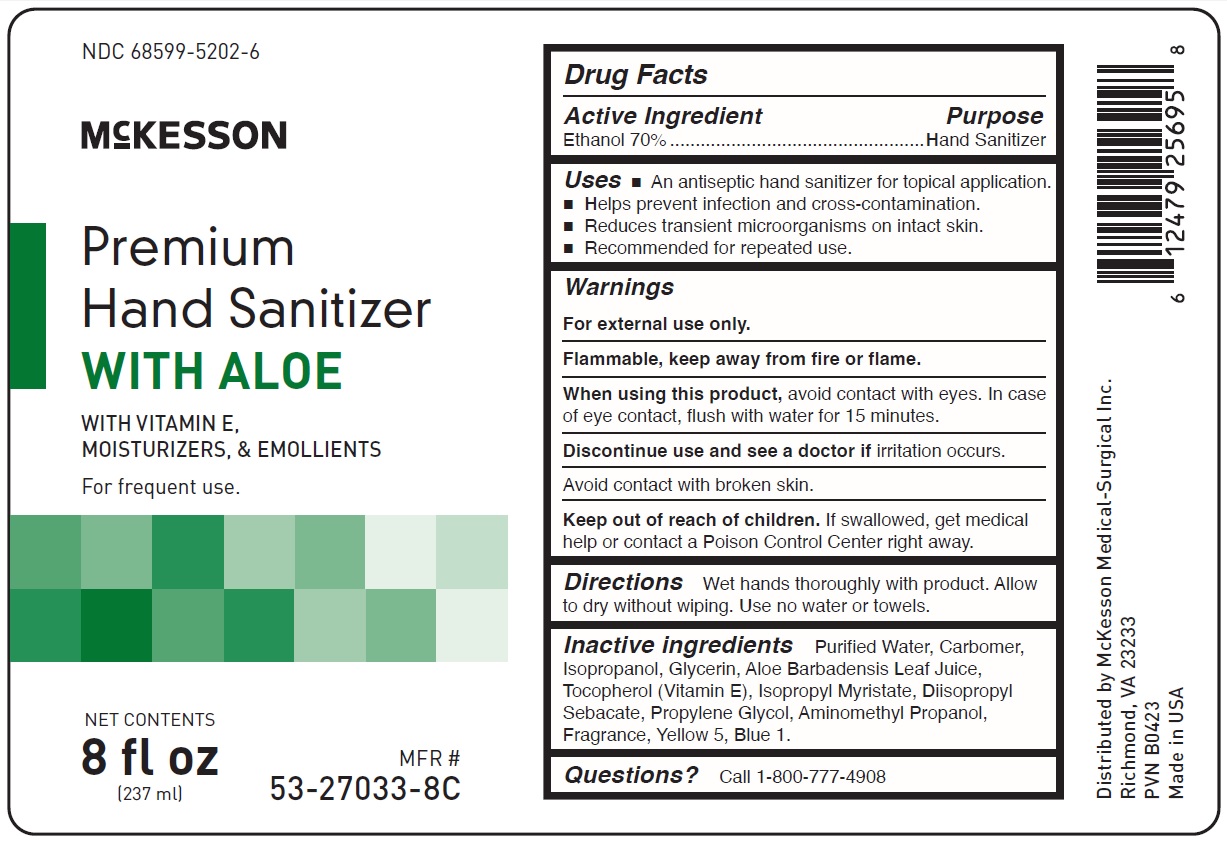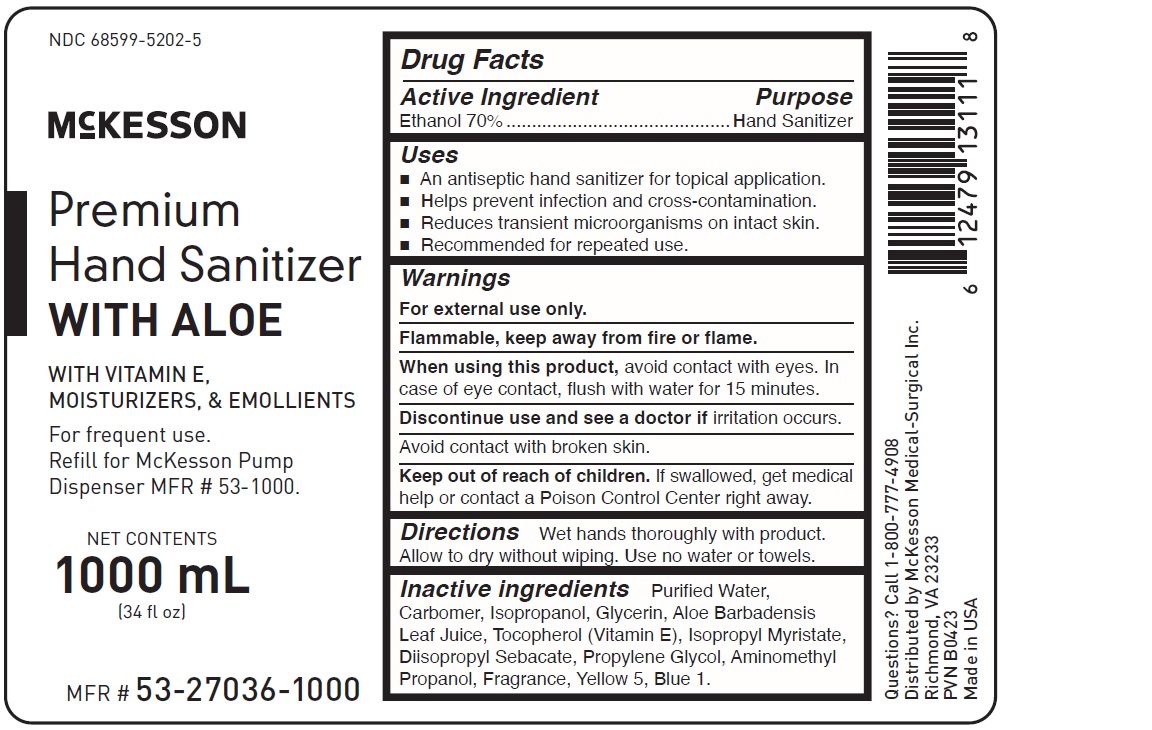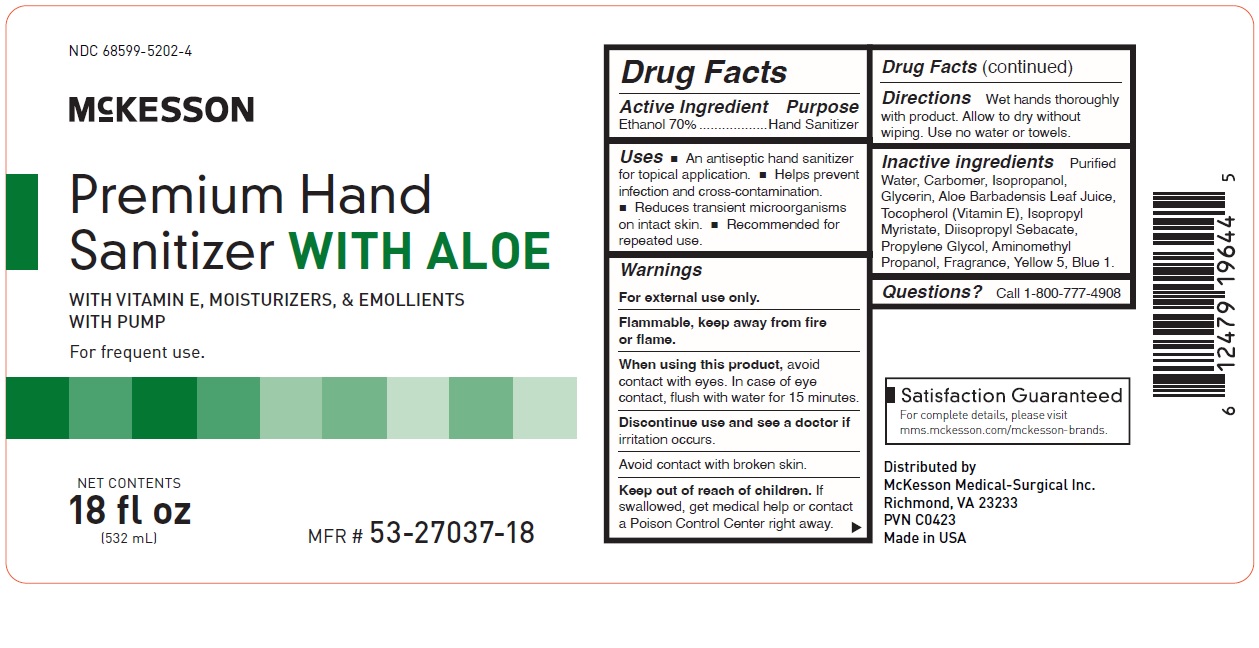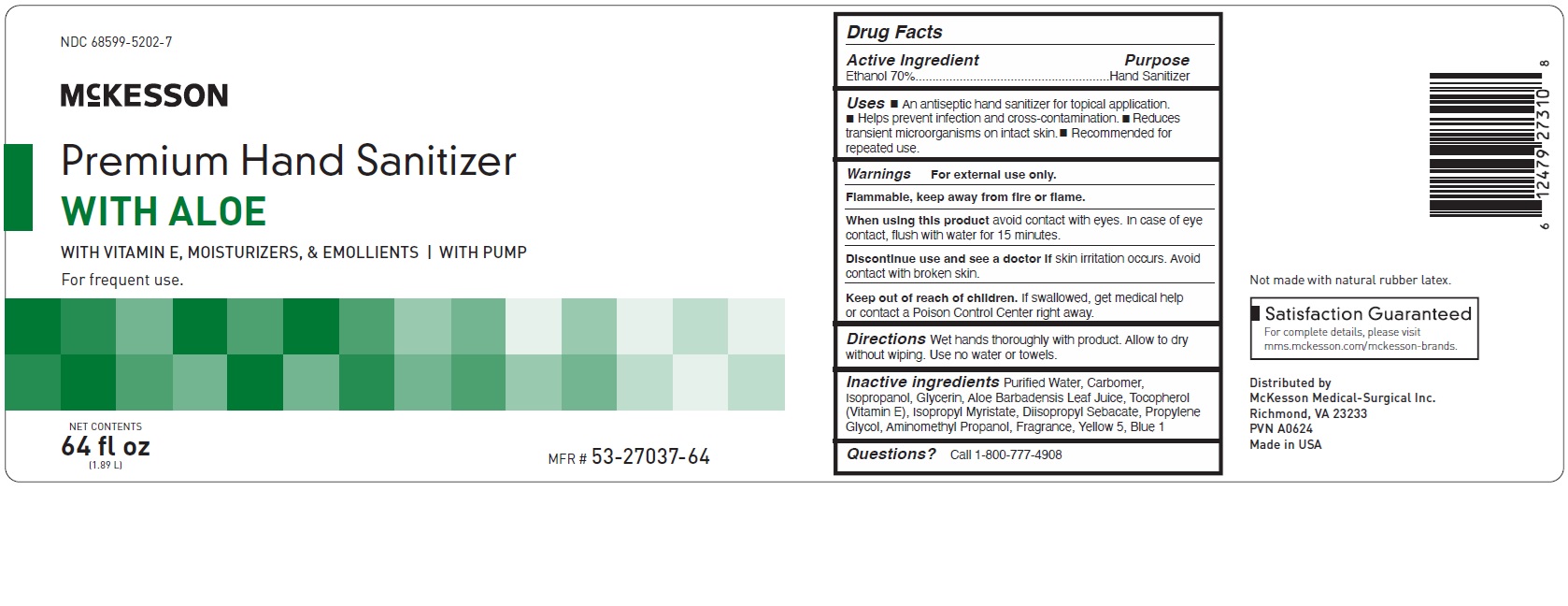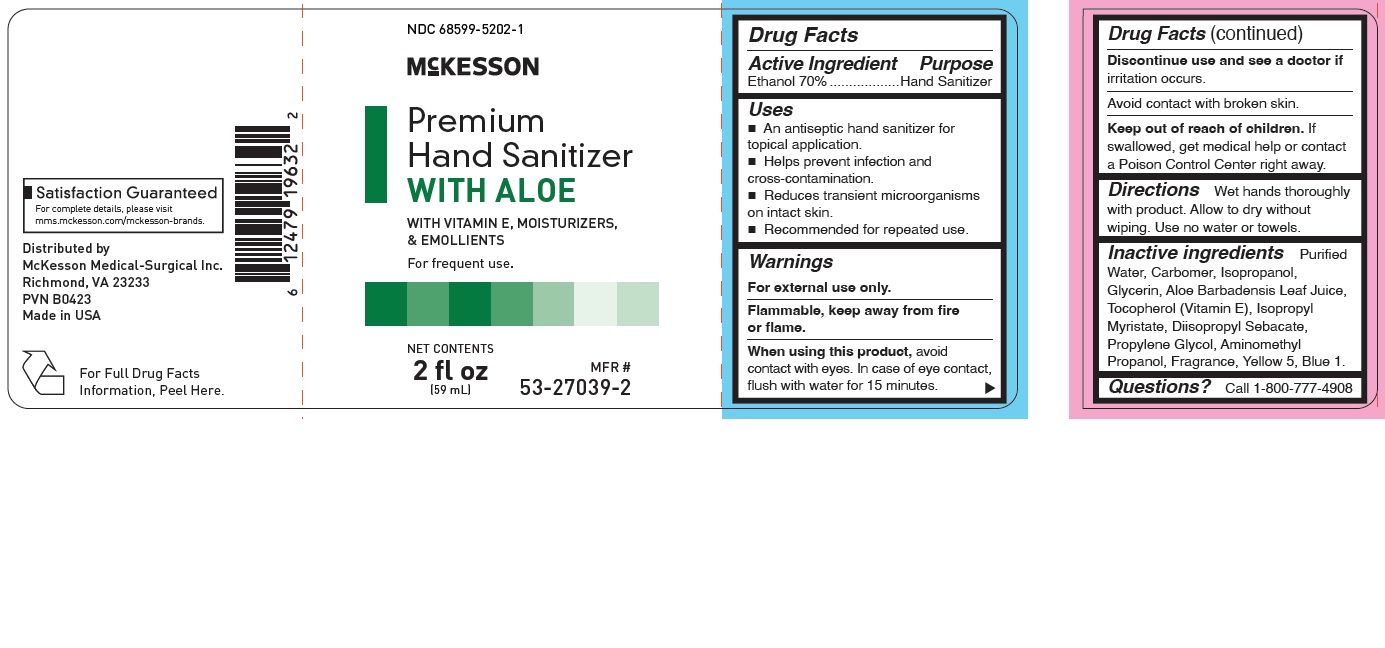 DRUG LABEL: Premium Hand Sanitizer with Aloe
NDC: 68599-5202 | Form: GEL
Manufacturer: MCKESSON MEDICAL-SURGICAL INC.
Category: otc | Type: HUMAN OTC DRUG LABEL
Date: 20250818

ACTIVE INGREDIENTS: ALCOHOL 70 g/100 g
INACTIVE INGREDIENTS: WATER; CARBOMER COPOLYMER TYPE A; ISOPROPYL ALCOHOL; GLYCERIN; ALOE VERA LEAF; TOCOPHEROL; ISOPROPYL MYRISTATE; DIISOPROPYL SEBACATE; PROPYLENE GLYCOL; AMINOMETHYLPROPANOL; FD&C YELLOW NO. 5; FD&C BLUE NO. 1

IHand Sanitizer

Active Ingredient Purpose

Ethanol 70% ......................... hand sanitizer

Uses

- an antiseptic hand sanitizer for topical application
- helps prevent infection and cross-contamination
- reduces transient microorganisms on intact skin
- recommended for repeated use

Keep out of reach of children. If swallowed, get medical help or contact a Poison Control Center right away.

INDICATIONS AND USAGE

McKesson Premium Hand Sanitizer with Aloe

With Vitamin E, Moisturizers, & Emollients

for frequent use

Directions

Wet hands thoroughly with product. Allow to dry without wiping. Use no water or towels.

Warnings

For external use only.

Flammable, keep away from fire or flame.

When using this product avoid contact with eyes. In case of eye contact, flush with water for 15 minutes.

Discontinue use and see a doctor if irritation occurs.

Avoid contact with broken skin.

Inactive Ingredients

purified water, carbomer, isopropanol, glycerin, aloe barbadensis leaf juice, tocopherol (vitamin E), isopropyl myristate, diisopropyl sebacate, propylene glycol, aminomethyl propanol, fragrance, yellow 5, blue 1.